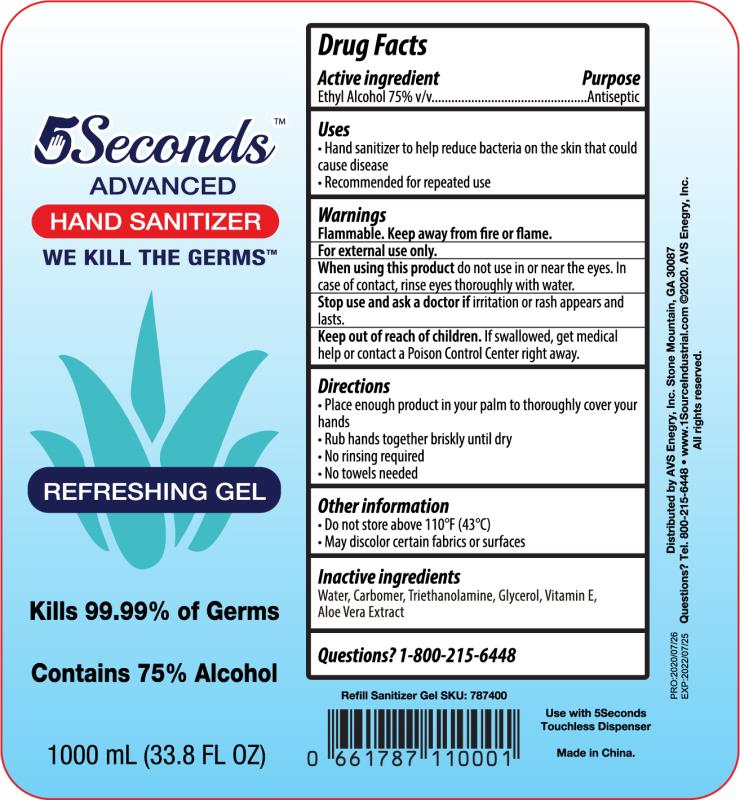 DRUG LABEL: 5Seconds Advanced Hand Sanitizer
NDC: 77871-004 | Form: GEL
Manufacturer: AVS Energy Inc
Category: otc | Type: HUMAN OTC DRUG LABEL
Date: 20201010

ACTIVE INGREDIENTS: ALCOHOL 75 mL/100 mL
INACTIVE INGREDIENTS: WATER; GLYCEROL FORMAL; ALOE VERA WHOLE; CARBOMER 940; .ALPHA.-TOCOPHEROL ACETATE; TROLAMINE

Active Ingredient(s)

Ethyl Alcohol 75% v/v

Purpose

Antiseptic

Use

Hand Sanitizer to help reduce bacteria on the skin that could cause disease

Recommended for repeated use

Warnings

For external use only.

Flammable. Keep away from fire or flame

When using this product, do not use in or near the eyes. In case of contact, rinse eyes thoroughly with water

Stop use and ask a doctor if irritation or rash appears and lasts

Keep out of reach of children. If swallowed, get medical help or contact a Poison Control Center right away.

Directions

Place enough products in your palm to thoroughly cover your hands

Rub hands together briskly until dry

No rinsing required

No towels needed

Other information

Do not store above 110F (43C)

May discolor certain fabrics or surfaces

Inactive ingredients

Water, Carbomer, Triethanolamine, Glycerol, Vitamin E, Aloe Vera Extract